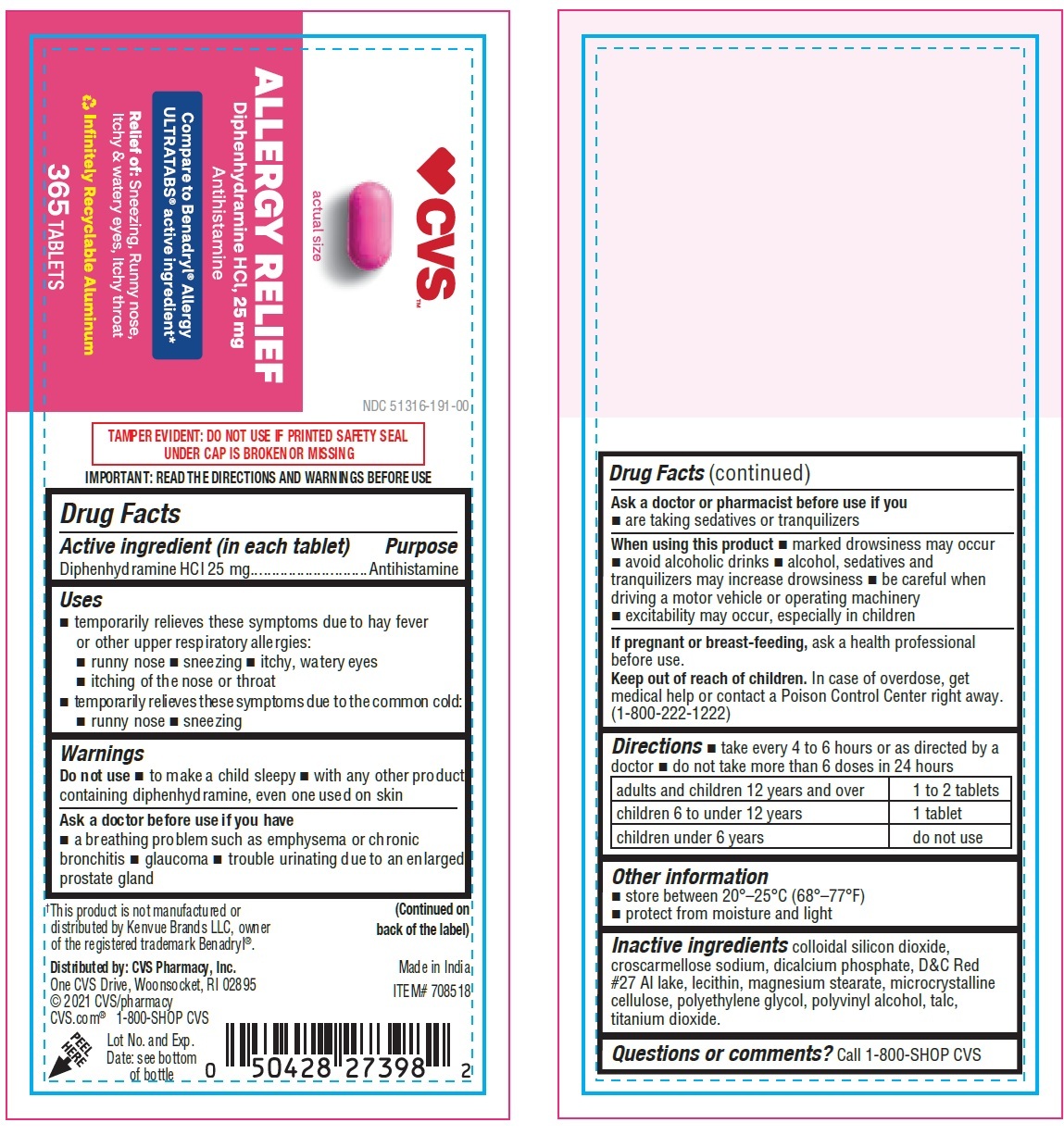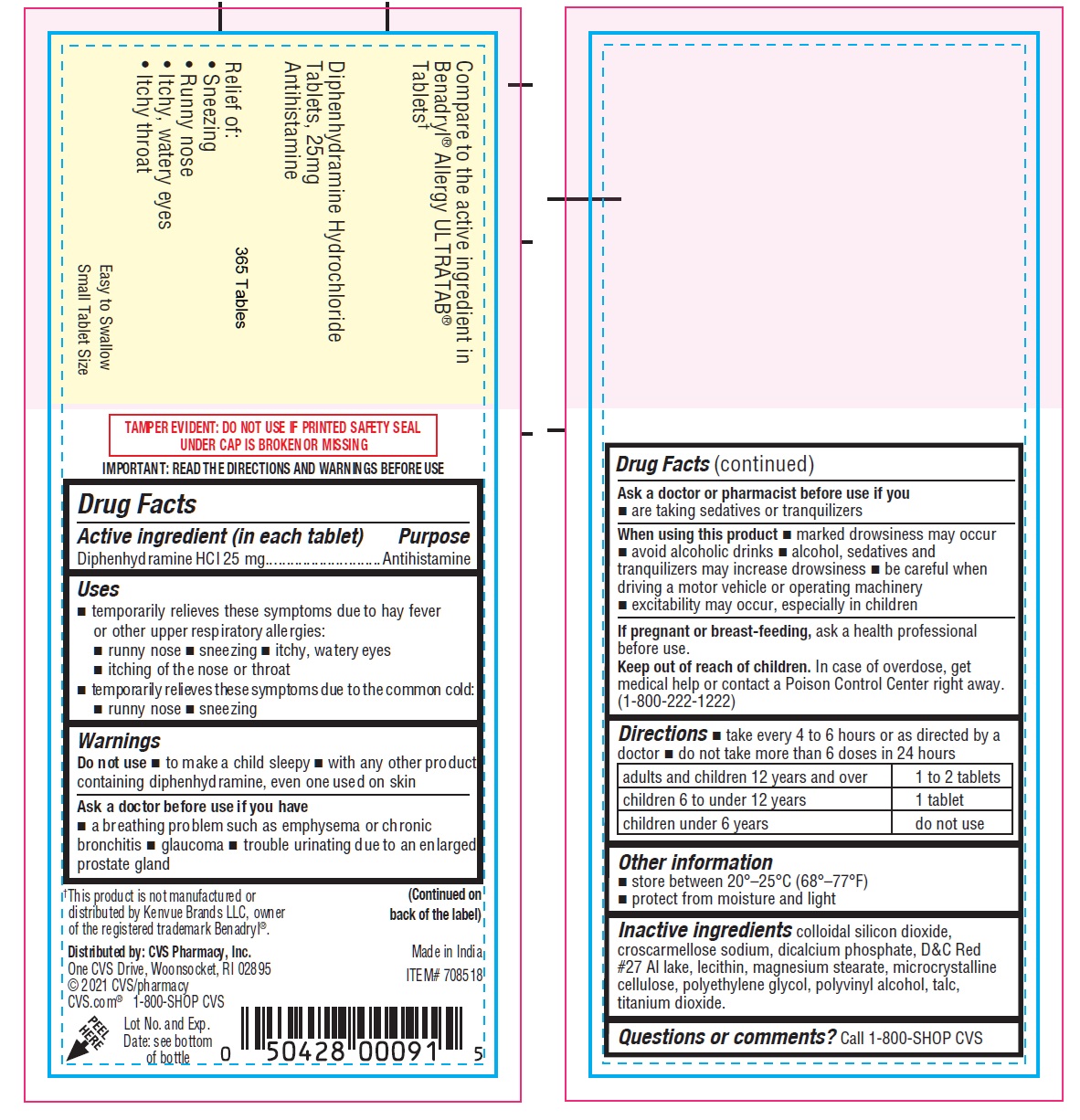 DRUG LABEL: CVS Diphenhydramine Hydrochloride
NDC: 51316-191 | Form: TABLET
Manufacturer: CVS Pharmacy
Category: otc | Type: HUMAN OTC DRUG LABEL
Date: 20251002

ACTIVE INGREDIENTS: DIPHENHYDRAMINE HYDROCHLORIDE 25 mg/1 1
INACTIVE INGREDIENTS: SILICON DIOXIDE; CROSCARMELLOSE SODIUM; ANHYDROUS DIBASIC CALCIUM PHOSPHATE; D&C RED NO. 27 ALUMINUM LAKE; MAGNESIUM STEARATE; MICROCRYSTALLINE CELLULOSE; POLYETHYLENE GLYCOL, UNSPECIFIED; POLYVINYL ALCOHOL, UNSPECIFIED; TALC; TITANIUM DIOXIDE

CVS Diphenhydramine Hydrochloride

Active ingredient (in each tablet)

Diphenhydramine Hydrochloride 25 mg

Purpose

Antihistamine

Uses

temporarily relieves these symptoms due to hay fever or other upper respiratory allergies: • runny nose • sneezing • itchy, watery eyes • itching of the nose or throat

• temporarily relieves these symptoms due to the common cold: • runny nose • sneezing

Warnings

Do not use

• to make a child sleepy • with any other product containing diphenhydramine, even one used on skin

Ask a doctor before use if you have

• a breathing problem such as emphysema or chronic bronchitis • glaucoma • trouble urinating due to an enlarged prostate gland

Ask a doctor or pharmacist before use if you

- are taking sedatives or tranquilizers

When using this product

- marked drowsiness may occur
- avoid alcoholic drinks
- alcohol, sedatives and tranquilizers may increase drowsiness
- be careful when driving a motor vehicle or operating machinery
- excitability may occur, especially in children

If pregnant or breast-feeding,

ask a health professional before use

Keep out of reach of children.

In case of overdose, get medical help or contact a Poison Control Center right away. (1-800-222-1222)

Directions

- take every 4 to 6 hours or as directed by a doctor
- do not take more than 6 doses in 24 hours

adults and children 12 years and over | 1 to 2 tablets
children 6 to under 12 years | 1 tablet
children under 6 years | do not use

Other information

- store between 20°–25°C (68°–77°F)
- protect from moisture and light

Inactive ingredients

colloidal silicon dioxide, croscarmellose sodium, dicalcium phosphate, D&C Red #27 Al lake, lecithin, magnesium stearate, microcrystalline cellulose, polyethylene glycol, polyvinyl alcohol, talc, titanium dioxide.

Questions or comments?

Call 1-800-SHOP CVS